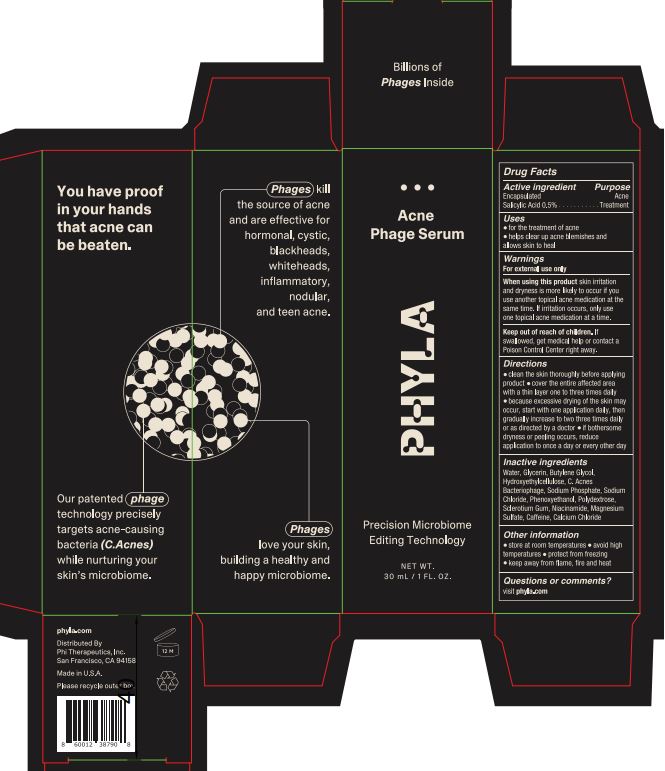 DRUG LABEL: Acne Phage Serum
NDC: 62742-4268 | Form: CREAM
Manufacturer: Allure Labs
Category: otc | Type: HUMAN OTC DRUG LABEL
Date: 20240926

ACTIVE INGREDIENTS: SALICYLIC ACID 0.5 g/100 g
INACTIVE INGREDIENTS: WATER; NIACINAMIDE; POLYDEXTROSE; MAGNESIUM SULFATE, UNSPECIFIED; PHENOXYETHANOL; BACTERIOPHAGE PHI X174; GLYCERIN; SODIUM CHLORIDE; BETASIZOFIRAN; CAFFEINE; BUTYLENE GLYCOL; HYDROXYETHYL CELLULOSE, UNSPECIFIED; SODIUM PHOSPHATE; CALCIUM CHLORIDE

Drug Facts

Active ingredient : Encapsulated Salicylic Acid 0.5%

Purpose: Acen Treatment

Uses:

For the treatment of acne
Help clear up acne blemishes and allows skin to heal

WARNINGS

Warning: For external use only

DO NOT USE

If you use another topical acne medication at the same time. If irritation occurs, only use one topical acne medication at a time

When using this product skin irritation and dryness is more likely to occur if you use another topical acne medication at the same time. If irritation occurs, only use one topical acne medication at a time

STOP USE

If irritation occurs

Keep out of reach of children. If swallowed, get medical help or contact a Poison Control Center right away.

Other information:

Store at room temperatures
Avoid high temperature
Protect from freezing
Keep away from flame, fire and heat

DOSAGE AND ADMINISTRATION

Direction:

Clean the skin thoroughly before applying product
Cover the entire affected area with the thin layer one to three time daily
Because excessive drying of the skin may ocure, start with one application daily, then gradually increases to two three time daily or as directed by a doctor
If bothersome dryness or peeling occurs, reduce application to once a day or every other day

Inactive ingredient: Water, Glycerin, Butylene Glycol, Hydroxyethylcellulose, C.Acnes Bacteriophage, Sodium Phosphate, Sodium Chloride, Phenoxyethanol, Polydextrose, Sclerotium Gum, Niacinamide, Magnesium Sulfate, Caffeine, Calcium Chloride